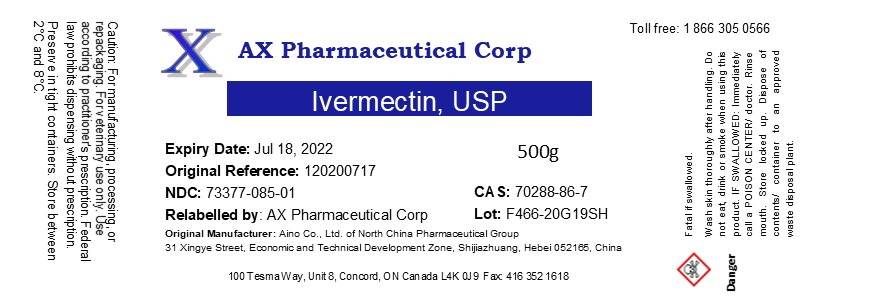 DRUG LABEL: Ivermectin
NDC: 73377-085 | Form: POWDER
Manufacturer: AX Pharmaceutical Corp
Category: other | Type: BULK INGREDIENT
Date: 20210408

ACTIVE INGREDIENTS: IVERMECTIN 1 g/1 g

Ivermectin